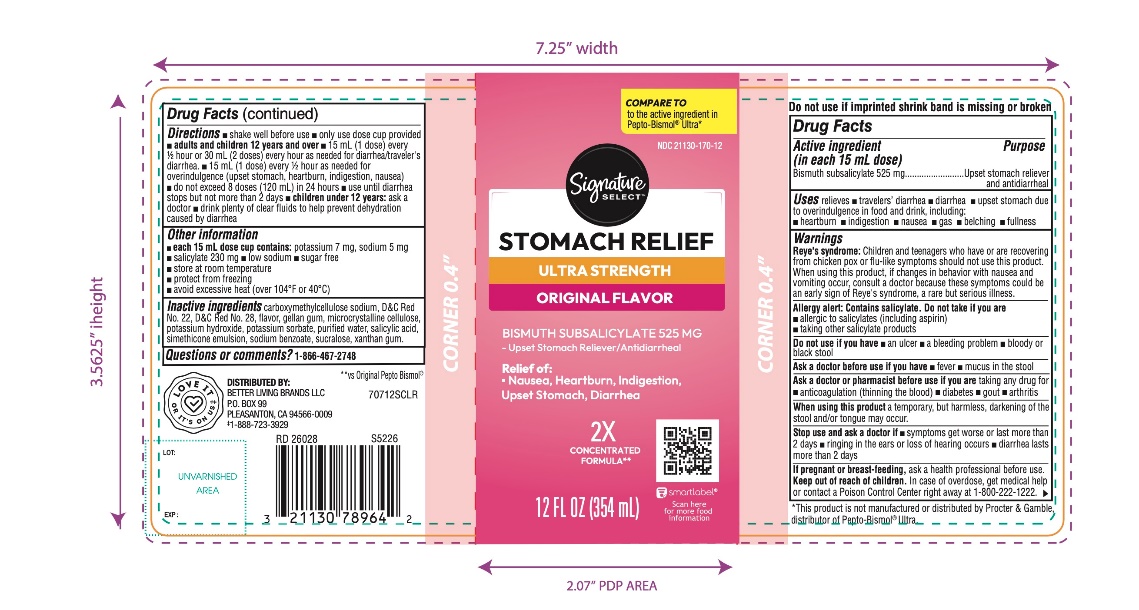 DRUG LABEL: SIGNATURE CARE
NDC: 21130-193 | Form: SUSPENSION
Manufacturer: SAFEWAY
Category: otc | Type: HUMAN OTC DRUG LABEL
Date: 20260220

ACTIVE INGREDIENTS: BISMUTH SUBSALICYLATE 525 mg/15 mL
INACTIVE INGREDIENTS: CARBOXYMETHYLCELLULOSE SODIUM, UNSPECIFIED; D&C RED NO. 22; D&C RED NO. 28; GELLAN GUM (LOW ACYL); MICROCRYSTALLINE CELLULOSE; POTASSIUM HYDROXIDE; POTASSIUM SORBATE; WATER; SALICYLIC ACID; DIMETHICONE, UNSPECIFIED; SODIUM BENZOATE; SUCRALOSE; XANTHAN GUM

Signature SELECT Ultra Strength Stomach Relief Drug Facts

Active ingredient (in each 15 mL dose)

Bismuth subsalicylate 525 mg

Purposes

Upset stomach reliever and antidiarrheal

Uses

relieves

- travelers’ diarrhea
- diarrhea
- upset stomach due to overindulgence in food and drink, including:
- heartburn
- indigestion
- nausea
- gas
- belching
- fullness

Warnings

Reye’s syndrome: Children and teenagers who have or are recovering from chicken pox or flu-like symptoms should not use this product. When using this product, if changes in behavior with nausea or vomiting occur, consult a doctor because these symptoms could be an early sign of Reye’s syndrome, a rare but serious illness.

Allergy alert: Contains salicylate. Do not take if you are

- allergic to salicylates (including aspirin)
- taking other salicylate products

Do not use if you have

- an ulcer
- a bleeding problem
- bloody or black stool

Ask a doctor before use if you have

- fever
- mucus in the stool

Ask a doctor or pharmacist before use if you are

taking any drug for

- anticoagulation (thinning the blood)
- diabetes
- gout
- arthritis

When using this product

a temporary, but harmless, darkening of the stool and/or tongue may occur

Stop use and ask a doctor if

- symptoms get worse or last more than 2 days
- ringing in the ears or loss of hearing occurs
- diarrhea lasts more than 2 days

If pregnant or breast-feeding,

ask a health professional before use.

Keep out of reach of children.

In case of overdose, get medical help or contact a Poison Control Center right away at 1-800-222-1222.

Directions

- shake well before use
- only use dose cup provided
- adults and children 12 years and over:
- 15 mL (1 dose) every ½ hour or 30 mL (2 doses) every hour as needed for diarrhea/traveler’s diarrhea
- 15 mL (1 dose) every ½ hour as needed overindulgence (upset stomach, heartburn, indigestion, nausea)
- do not exceed 8 doses (120 mL) in 24 hours
- use until diarrhea stops but not more than 2 days
- children under 12 years: ask a doctor
- drink plenty of clear fluids to help prevent dehydration caused by diarrhea

Other information

- each 15 mL dose cup contains: potassium 7 mg, sodium 5 mg
- salicylate 230 mg
- low sodium
- sugar free
- store at room temperature
- protect from freezing
- avoid excessive heat (over 104°F or 40°C)

Inactive ingredients

carboxymethylcellulose sodium, D&C Red No. 22, D&C Red No. 28, flavor, gellan gum, microcrystalline cellulose, potassium hydroxide, potassium sorbate, purified water, salicylic acid, simethicone emulsion, sodium benzoate, sucralose, xanthan gum

Questions or comments?

1-866-467-2748

Do not use if imprinted shrink band is missing or broken.

Principal Display Panel

Signature SELECT™

NDC 21130-193-12

COMPARE TO the active ingredient in Pepto-Bismol® *

STOMACH RELIEF

ULTRA STRENGTH

ORIGINAL FLAVOR

Bismuth Subsalicylate 525 MG

Upset Stomach Reliever/Antidiarrheal

Relief of:

- Nausea, Heartburn, Indigestion, Upset Stomach, Diarrhea

12 FL. OZ. (354 mL)

2X CONCENTRATED FORMULA**

Distributed by: BETTER LIVING BRANDS LLC

P.O. BOX 99

PLEASANTON, CA 94566-0009

‡1-888-723-3929

**vs Original Pepto Bismol®

*This product is not manufactured or distributed by Procter & Gamble, distributor of Pepto-Bismol® Ultra.